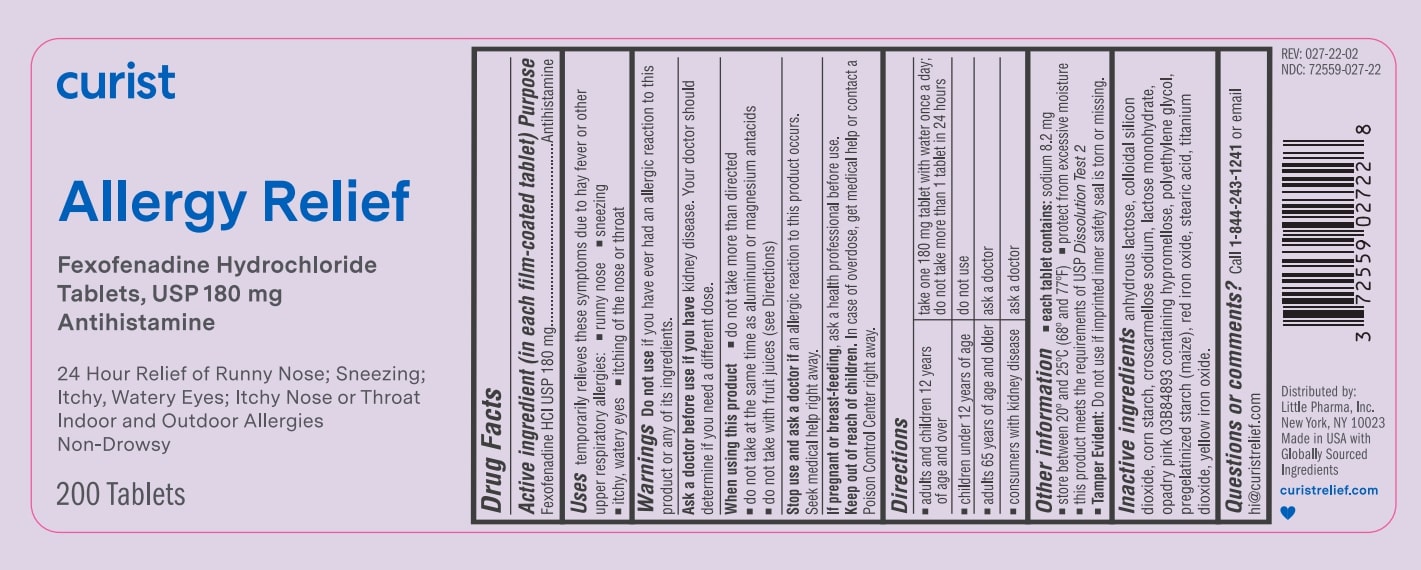 DRUG LABEL: Curist Allergy Relief
NDC: 72559-027 | Form: TABLET
Manufacturer: Little Pharma, Inc.
Category: otc | Type: HUMAN OTC DRUG LABEL
Date: 20241115

ACTIVE INGREDIENTS: FEXOFENADINE HYDROCHLORIDE 180 mg/1 1
INACTIVE INGREDIENTS: TITANIUM DIOXIDE; SILICON DIOXIDE; STARCH, CORN; LACTOSE MONOHYDRATE; STEARIC ACID; FERRIC OXIDE YELLOW; HYPROMELLOSE, UNSPECIFIED; POLYETHYLENE GLYCOL, UNSPECIFIED; FERRIC OXIDE RED; ANHYDROUS LACTOSE; CROSCARMELLOSE SODIUM

Curist Allergy Relief (fexofenadine hcl 180 mg)

Drug Facts

Active ingredient (in each film-coated tablet)

Fexofenadine HCl USP 180 mg

Purpose

Antihistamine

Uses

temporarily relieves these symptoms due to hay fever or other upper respiratory allergies:

- runny nose
- sneezing
- itchy, watery eyes
- itching of the nose or throat

Warnings

Do not use if you have ever had an allergic reaction to this product or any of its ingredients.

Ask a doctor before use if you have kidney disease. Your doctor should determine if you need a different dose.

When using this product

- do not take more than directed
- do not take at the same time as aluminum or magnesium antacids
- do not take with fruit juices (see Directions)

Stop use and ask a doctor if an allergic reaction to this product occurs. Seek medical help right away.

PREGNANCY OR BREAST FEEDING

If pregnant or breast-feeding, ask a health professional before use.

Keep out of reach of children. In case of overdose, get medical help or contact a Poison Control Center right away.

Directions

- adults and children 12 years of age and over | take one 180 mg tablet with water once a day;; do not take more than 1 tablet in 24 hours
- children under 12 years of age | do not use
- adults 65 years of age and older | ask a doctor
- consumers with kidney disease | ask a doctor

Other information

- each tablet contains: sodium 8.2 mg
- store between 20º and 25ºC (68º and 77ºF)
- protect from excessive moisture
- this product meets the requirements of USP Dissolution Test 2
- Tamper Evident: Do not use if imprinted inner safety seal is torn or missing.

Inactive ingredients

anhydrous lactose, colloidal silicon dioxide, corn starch, croscarmellose sodium, lactose monohydrate, opadry pink 03B84893 containing hypromellose, polyethylene glycol, pregelatinized starch (maize), red iron oxide, stearic acid, titanium dioxide, yellow iron oxide.

Questions or comments?

Call 1-844-243-1241 or email hi@curistrelief.com

Rev: 027-22-01

Distributed by:

Little Pharma, Inc.

New York, NY 10023

Made in USA with

Globally Sourced Ingredients

curistrelief.com

PACKAGE LABEL

curist

Allergy Relief

Fexofenadine Hydrochloride

Tablets, USP 180 mg

Antihistamine

24 Hour Reilef of Runny Nose; Sneezing;

Itchy, Watery Eyes; Itchy Nose or Throat

Indoor and Outdoor Allergies

Non-Drowsy

200 Tablets